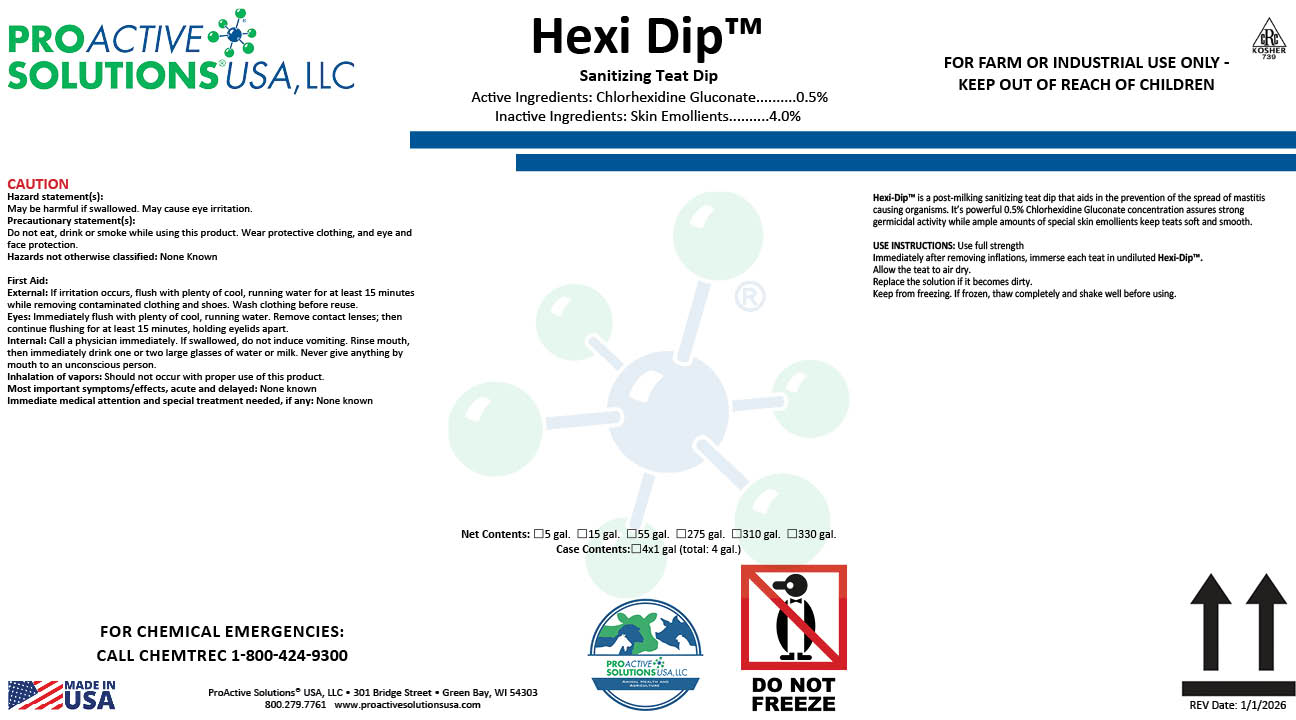 DRUG LABEL: Hexi Dip
NDC: 63927-4180 | Form: LIQUID
Manufacturer: ProActive Solutions USA, LLC
Category: animal | Type: OTC ANIMAL DRUG LABEL
Date: 20260217

ACTIVE INGREDIENTS: CHLORHEXIDINE GLUCONATE 0.5 kg/100 kg

Hexi Dip

Hexi Dip

Hexi-Dip™ is a post-milking sanitizing teat dip that aids in the prevention of the spread of mastitis causing organisms. It’s powerful 0.5% Chlorhexidine Gluconate concentration assures strong germicidal activity while ample amounts of special skin emollients keep teats soft and smooth.

USE INSTRUCTIONS: Use full strength
Immediately after removing inflations, immerse each teat in undiluted Hexi-Dip™.
Allow the teat to air dry.
Replace the solution if it becomes dirty.
Keep from freezing. If frozen, thaw completely and shake well before using.

Active Ingredients: Chlorhexidine Gluconate..........0.5%
Inactive Ingredients: Skin Emollients..........4.0%

Hazard statement(s):
May be harmful if swallowed. May cause eye irritation.
Precautionary statement(s):
Do not eat, drink or smoke while using this product. Wear protective clothing, and eye and face protection.
Hazards not otherwise classified: None Known

First Aid:
External: If irritation occurs, flush with plenty of cool, running water for at least 15 minutes while removing contaminated clothing and shoes. Wash clothing before reuse.
Eyes: Immediately flush with plenty of cool, running water. Remove contact lenses; then continue flushing for at least 15 minutes, holding eyelids apart.
Internal: Call a physician immediately. If swallowed, do not induce vomiting. Rinse mouth, then immediately drink one or two large glasses of water or milk. Never give anything by mouth to an unconscious person.
Inhalation of vapors: Should not occur with proper use of this product.
Most important symptoms/effects, acute and delayed: None known
Immediate medical attention and special treatment needed, if any: None known